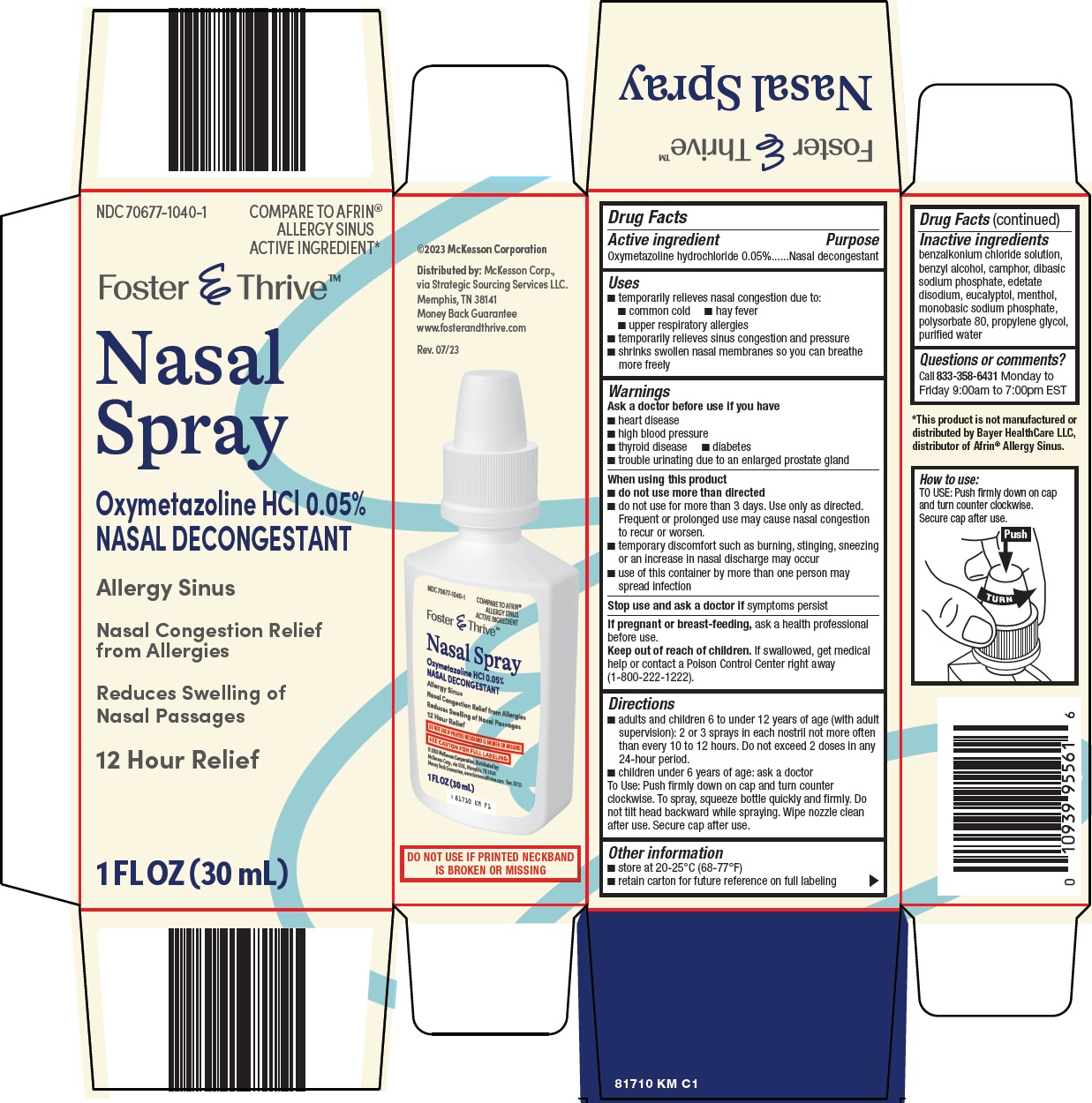 DRUG LABEL: foster and thrive nasal
NDC: 70677-1040 | Form: SPRAY
Manufacturer: Strategic Sourcing Services LLC
Category: otc | Type: HUMAN OTC DRUG LABEL
Date: 20241017

ACTIVE INGREDIENTS: OXYMETAZOLINE HYDROCHLORIDE 0.05 g/100 mL
INACTIVE INGREDIENTS: BENZALKONIUM CHLORIDE; BENZYL ALCOHOL; SODIUM PHOSPHATE, DIBASIC, UNSPECIFIED FORM; EDETATE DISODIUM; EUCALYPTOL; MENTHOL, UNSPECIFIED FORM; SODIUM PHOSPHATE, MONOBASIC, UNSPECIFIED FORM; POLYSORBATE 80; PROPYLENE GLYCOL; WATER

McKesson Nasal Spray Drug Facts

Active ingredient

Oxymetazoline hydrochloride 0.05%

Purpose

Nasal decongestant

Uses

- temporarily relieves nasal congestion due to:
- common cold
- hay fever
- upper respiratory allergies
- temporarily relieves sinus congestion and pressure
- shrinks swollen nasal membranes so you can breathe more freely

Warnings

Ask a doctor before use if you have

- heart disease
- high blood pressure
- thyroid disease
- diabetes
- trouble urinating due to an enlarged prostate gland

When using this product

- do not use more than directed
- do not use for more than 3 days. Use only as directed. Frequent or prolonged use may cause nasal congestion to recur or worsen.
- temporary discomfort such as burning, stinging, sneezing or an increase in nasal discharge may occur
- use of this container by more than one person may spread infection

Stop use and ask a doctor if

symptoms persist

If pregnant or breast-feeding,

ask a health professional before use.

Keep out of reach of children.

If swallowed, get medical help or contact a Poison Control Center right away (1-800-222-1222).

Directions

- adults and children 6 to under 12 years of age (with adult supervision): 2 or 3 sprays in each nostril not more often than every 10 to 12 hours. Do not exceed 2 doses in any 24-hour period.
- children under 6 years of age: ask a doctor

To Use: Push firmly down on cap and turn counter clockwise. To spray, squeeze bottle quickly and firmly. Do not tilt head backward while spraying. Wipe nozzle clean after use. Secure cap after use.

Other information

- store at 20-25°C (68-77°F)
- retain carton for future reference on full labeling

Inactive ingredients

benzalkonium chloride solution, benzyl alcohol, camphor, dibasic sodium phosphate, edetate disodium, eucalyptol, menthol, monobasic sodium phosphate, polysorbate 80, propylene glycol, purified water

Questions or comments?

Call 833-358-6431 Monday to Friday 9:00am to 7:00pm EST

Principal Display Panel

COMPARE TO AFRIN® ALLERGY SINUS ACTIVE INGREDIENT

Foster & Thrive™

Nasal Spray

Oxymetazoline HCl 0.05%

NASAL DECONGESTANT

Allergy Sinus

Nasal Congestion Relief from Allergies

Reduces Swelling of Nasal Passages

12 Hour Relief

1 FL OZ (30 mL)